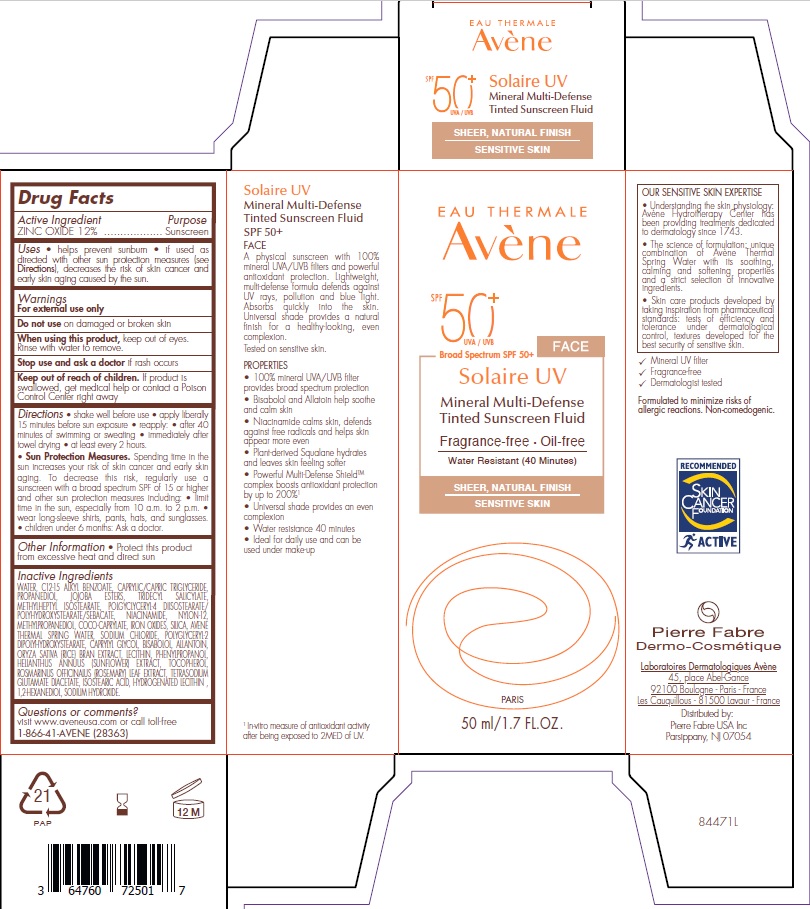 DRUG LABEL: Avene Solaire UV Tinted Mineral Sunscreen
NDC: 64760-725 | Form: LOTION
Manufacturer: Pierre Fabre USA Inc.
Category: otc | Type: HUMAN OTC DRUG LABEL
Date: 20240119

ACTIVE INGREDIENTS: ZINC OXIDE 120 mg/1 mL
INACTIVE INGREDIENTS: POLYGLYCERYL-2 DIPOLYHYDROXYSTEARATE; RICE BRAN OIL; TETRASODIUM GLUTAMATE DIACETATE; WATER; ROSEMARY; LEVOMENOL; METHYLHEPTYL ISOSTEARATE; NYLON-12; FERRIC OXIDE YELLOW; ALKYL (C12-15) BENZOATE; NIACINAMIDE; ALLANTOIN; PHENYLPROPANOL; HELIANTHUS ANNUUS FLOWERING TOP; TOCOPHEROL; ISOSTEARIC ACID; LECITHIN, SOYBEAN; 1,2-HEXANEDIOL; SODIUM HYDROXIDE; CAPRYLYL GLYCOL; FERROSOFERRIC OXIDE; HYDROGENATED SOYBEAN LECITHIN; FERRIC OXIDE RED; SILICON DIOXIDE; MEDIUM-CHAIN TRIGLYCERIDES; PROPANEDIOL; JOJOBA OIL; TRIDECYL SALICYLATE; METHYLPROPANEDIOL; COCO-CAPRYLATE; SODIUM CHLORIDE

Avene Solaire UV Tinted Mineral Sunscreen SPF 50 PLUS

Active ingredient

Zinc Oxide 12%

Purpose

Sunscreen

Uses

• helps prevent sunburn • if used as directed with other sun protection measures (see Directions), decreases the risk of skin cancer and early skin aging caused by the sun.

Warnings

For external use only

Do not use

on damaged or broken skin.

When using this product,

keep out of eyes. Rinse with water to remove.

Stop use and ask a doctor

if rash occurs.

Keep out of reach of children.

If product is swallowed, get medical help or contact a Poison Control Center right away.

Directions

• shake well before use • apply liberally 15 minutes before sun exposure • reapply: • after 40 minutes of swimming or sweating • immediately after towel drying • at least every 2 hours.

• Sun Protection Measures. Spending time in the sun increases your risk of skin cancer and early skin aging. To decrease this risk, regularly use a sunscreen with a broad spectrum SPF of 15 or higher and other sun protection measures including: • limit time in the sun, especially from 10 a.m to 2 p.m. • wear long-sleeve shirts, pants, hats, and sunglasses. • children under 6 months: Ask a doctor.

Other information

• Protect this product from excessive heat and direct sun.

Inactive ingredients

WATER, C12-15 ALKYL BENZOATE, CAPRYLIC/CAPRIC TRIGLYCERIDE, PROPANEDIOL, JOJOBA ESTERS, TRIDECYL SALICYLATE, METHYLHEPTYL ISOSTEARATE, POLYGLYCERYL-4 DIISOSTEARATE/POLYHYDROXYSTEARATE/SEBACATE, NIACINAMIDE, NYLON-12, METHYLPROPANEDIOL, COCO-CAPRYLATE, IRON OXIDES, SILICA, AVENE THERMAL SPRING WATER, SODIUM CHLORIDE, POLYGLYCERYL-2 DIPOLYHYDROXYSTEARATE, CAPRYLYL GLYCOL, BISABOLOL, ALLANTOIN, ORYZA SATIVA (RICE) BRAN EXTRACT, LECITHIN, PHENYLPROPANOL, HELIANTHUS ANNUUS (SUNFLOWER) EXTRACT, TOCOPHEROL, ROSMARINUS OFFICINALIS (ROSEMARY) LEAF EXTRACT, TETRASODIUM GLUTAMATE DIACETATE, ISOSTEARIC ACID, HYDROGENATED LECITHIN,1,2-HEXANEDIOL, SODIUM HYDROXIDE

Questions or comments?

visit www.aveneusa.com or call toll-free 1-866-41-AVENE (28363)

Principal Display Panel - 50 mL Carton

EAU THERMALE

Avene

SPF 50+

UVA/UVB

Broad Spectrum SPF 50+

Solaire UV

Mineral Multi-Defense

Tinted Sunscreen Fluid

Fragrance-Free • Oil-Free

Water Resistant (40-Minute)

Sheer, Natural Finish

Sensitive Skin

50 ml/1.7 FL. OZ.

Pierre Fabre

Dermo-Cosmetique

Laboratoires Dermatologiques Avène
45, place Abel-Gance
92100 Boulogne - Paris - France
Les Cauquillous - 81500 Lavaur - France
Distributed by:
Pierre Fabre USA Inc
Parsippany, NJ 07054